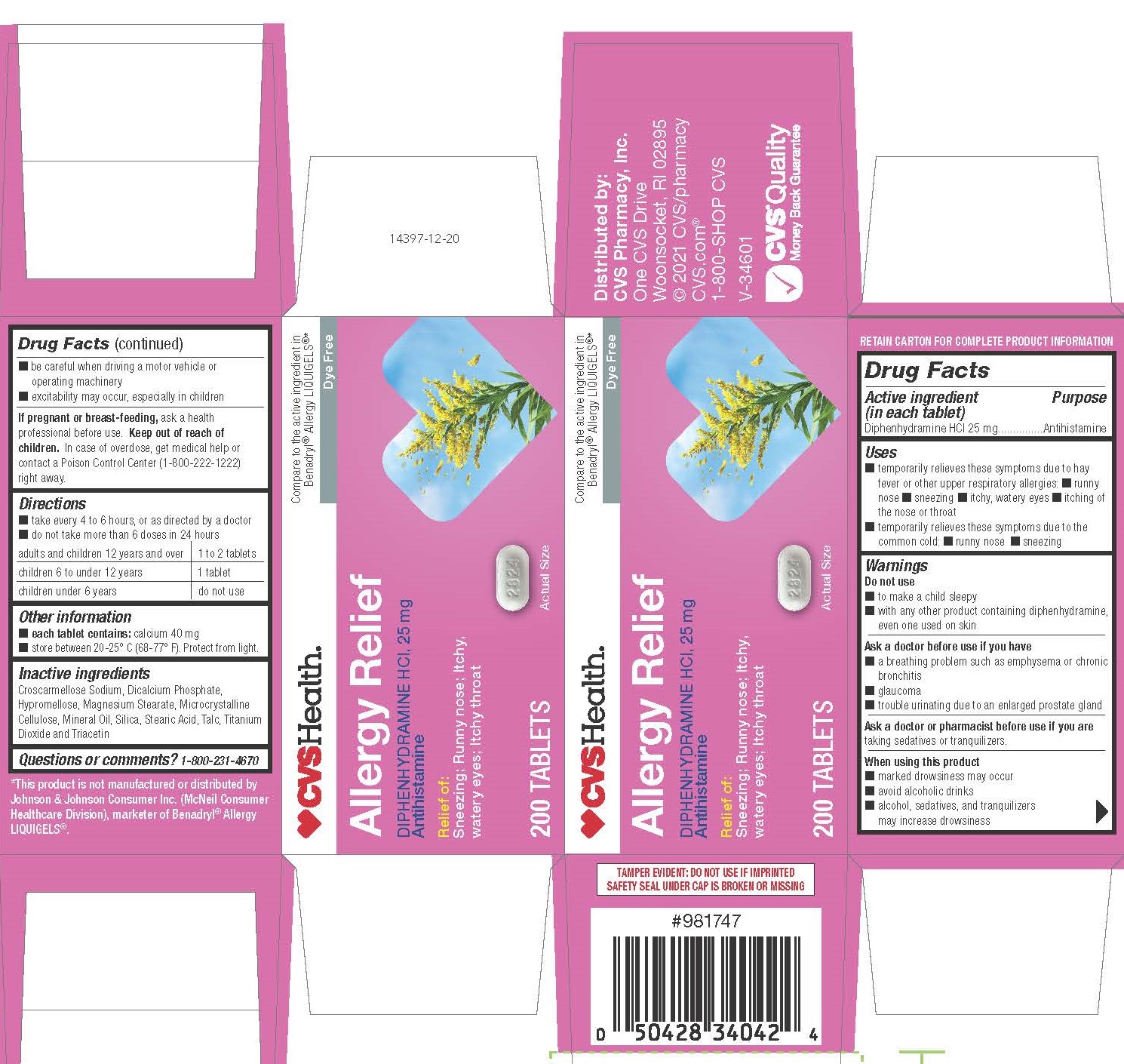 DRUG LABEL: Diphenhydramine Hydrochloride
NDC: 69842-981 | Form: TABLET, FILM COATED
Manufacturer: CVS Pharmacy, Inc
Category: otc | Type: HUMAN OTC DRUG LABEL
Date: 20241202

ACTIVE INGREDIENTS: DIPHENHYDRAMINE HYDROCHLORIDE 25 mg/1 1
INACTIVE INGREDIENTS: MAGNESIUM STEARATE; DIBASIC CALCIUM PHOSPHATE DIHYDRATE; MICROCRYSTALLINE CELLULOSE; SILICON DIOXIDE; TRIACETIN; STEARIC ACID; TALC; TITANIUM DIOXIDE; HYPROMELLOSES; CROSCARMELLOSE SODIUM; LIGHT MINERAL OIL

2834A-CVS

Drug Facts

Active ingredient (in each tablet)
Diphenhydramine HCl 25 mg

Purpose
Antihistamine

Uses

■ Temporarily relieves these symptoms due to hay fever or other upper respiratory allergies:

■ Runny nose

■ Sneezing

■ Itchy, watery eyes

■ Itching of the nose or throat

■ Temporarily relieves these symptoms due to the common cold: ■ Runny nose ■ Sneezing

WARNINGS

Do not use

■ To make a child sleepy
■ With any other product containing diphenhydramine, even one used on skin

Ask a doctor before use if you have

■ A breathing problem such as emphysema or chronic bronchitis
■ Glaucoma
■ Trouble urinating due to an enlarged prostate gland

Ask a doctor or pharmacist before use if you are

taking sedatives or tranquilizers.

When using this product

■ Marked drowsiness may occur
■ Avoid alcoholic drinks
■ Alcohol, sedatives, and tranquilizers may increase drowsiness

■ Be careful when driving a motor vehicle or operating machinery
■ Excitability may occur, especially in children

PREGNANCY OR BREAST FEEDING

If pregnant or breast-feeding, ask a health professional before use.

Keep out of reach of children.

OVERDOSAGE

In case of overdose, get medical help or contact a Poison Control Center (1-800-222-1222) right away.

Directions

■ Take every 4 to 6 hours, or as directed by a doctor
■ Do not take more than 6 times in 24 hours

Adults and children 12 years and over | 1 to 2 tablets
Children 6 to under 12 years | 1 tablet
Children under 6 years | do not use

Other information

■ Each tablet contains: calcium 37 mg
■ Store between 20-25° C (68-77° F). Protect from light.

INACTIVE INGREDIENT

Croscarmellose Sodium, Dicalcium Phosphate, Hypromellose, Magnesium Stearate, Microcrystalline Cellulose, Mineral Oil, Silica, Stearic Acid, Talc, Titanium Dioxide and Triacetin

Questions or comments?

1-800-231-4670

*This product is not manufactured or distributed by McNeil Consumer Healthcare, owner of the registered trademark Benadryl® Allergy LIQUIGELS®.

TAMPER EVIDENT: DO NOT USE IF IMPRINTED SAFETY SEAL UNDER CAP IS BROKEN OR MISSING

RETAIN CARTON FOR COMPLETE PRODUCT INFORMATION

Distributed by:
CVS Pharmacy, Inc.
One CVS Drive
Woonsocket, RI 02895
© 2020 CVS/pharmacy CVS.com®
1-800-SHOP CVS
Product of China
V-34601

PACKAGE LABEL

CVS Health

Compare to the active ingredient in Benadryl® Allergy LIQUIGELS®*

Allergy Relief

Diphehydramine HCl, 25 mg

Antihistamine

Relief of: Sneezing; Runny nose; Itchy,watery eyes; Itchy throat

200 Tablets